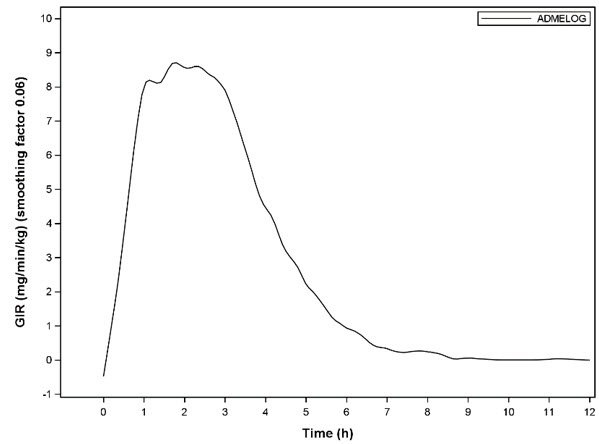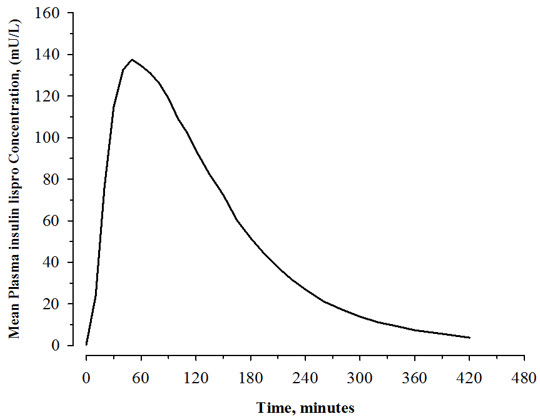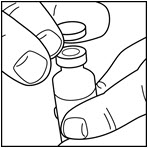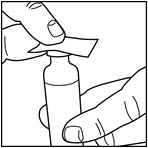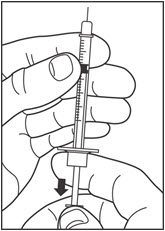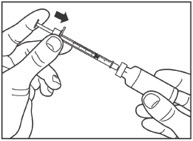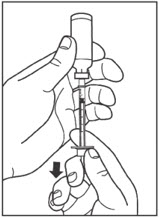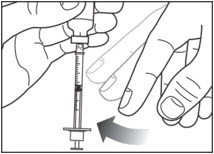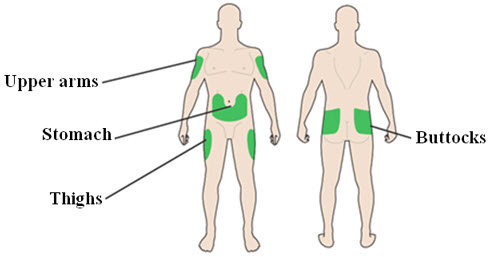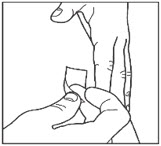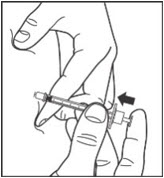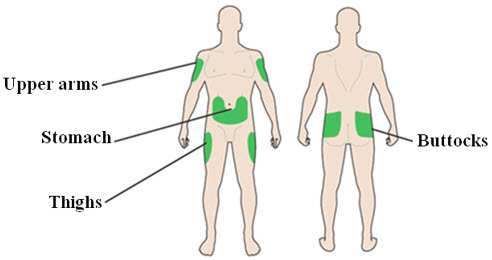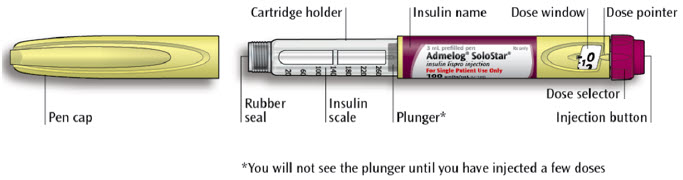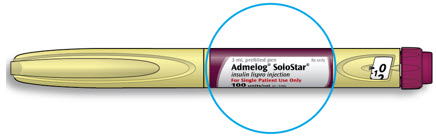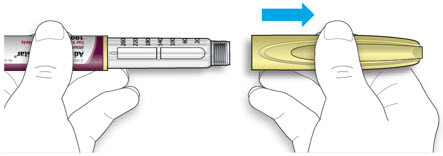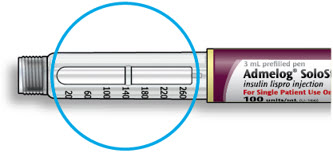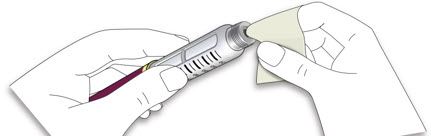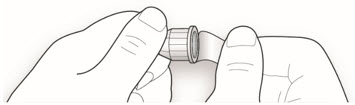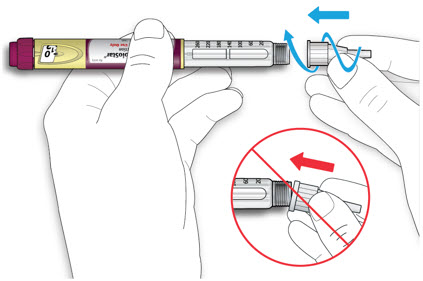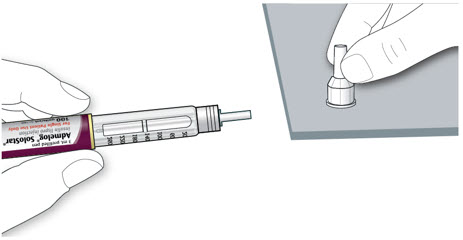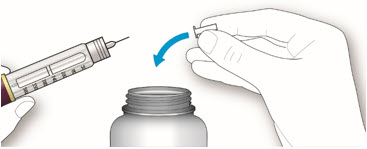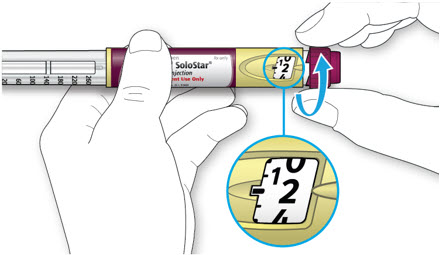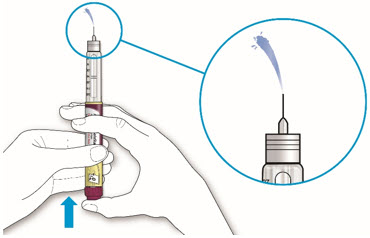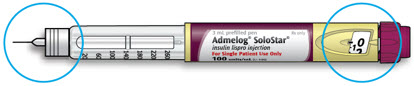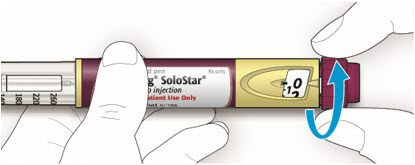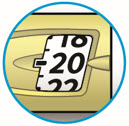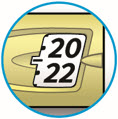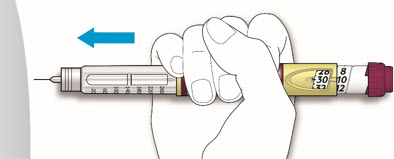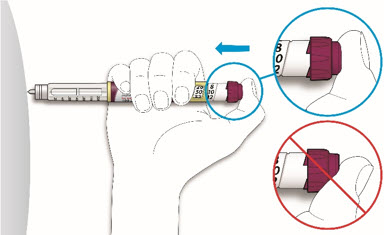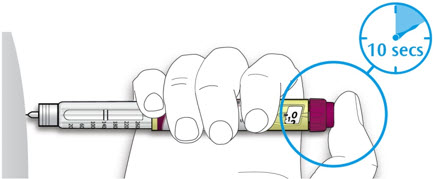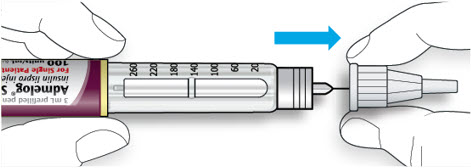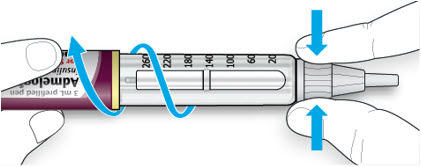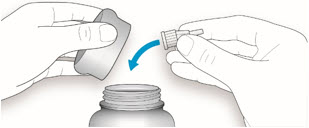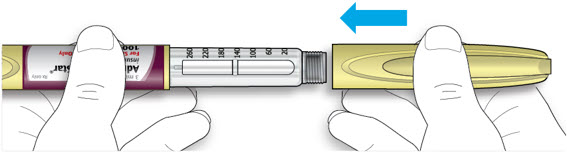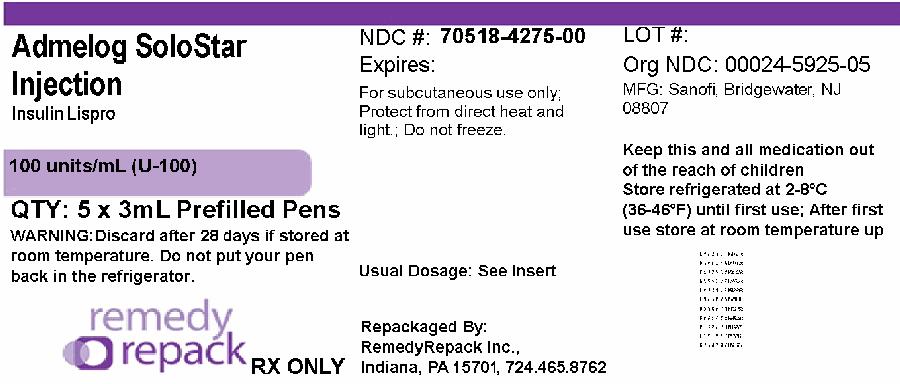 DRUG LABEL: ADMELOG
NDC: 70518-4275 | Form: INJECTION, SOLUTION
Manufacturer: REMEDYREPACK INC.
Category: prescription | Type: HUMAN PRESCRIPTION DRUG LABEL
Date: 20251001

ACTIVE INGREDIENTS: INSULIN LISPRO 100 U/1 mL
INACTIVE INGREDIENTS: GLYCERIN 16 mg/1 mL; SODIUM PHOSPHATE, DIBASIC, UNSPECIFIED FORM 1.88 mg/1 mL; METACRESOL 3.15 mg/1 mL; ZINC OXIDE 0.0197 mg/1 mL; WATER; HYDROCHLORIC ACID; SODIUM HYDROXIDE

HIGHLIGHTS OF PRESCRIBING INFORMATION

These highlights do not include all the information needed to use ADMELOG safely and effectively. See full prescribing information for ADMELOG®.
ADMELOG (insulin lispro) injection, for subcutaneous or intravenous use
Initial U.S. Approval: 2017

1 INDICATIONS AND USAGE

ADMELOG is a rapid-acting human insulin analog indicated to improve glycemic control in adult and pediatric patients with diabetes mellitus. (1)

2 DOSAGE AND ADMINISTRATION

- See Full Prescribing Information for important preparation and administration instructions. (2.1, 2.2, 2.3, 2.4)
- Rotate injection sites to reduce risk of lipodystrophy and localized cutaneous amyloidosis. (2.2)
- Subcutaneous injection (2.2):
  - Administer ADMELOG by subcutaneous injection into the abdominal wall, thigh, upper arm, or buttocks within 15 minutes before a meal or immediately after a meal.
  - Rotate injection sites to reduce risk of lipodystrophy and localized cutaneous amyloidosis.
- Continuous subcutaneous infusion (Insulin Pump) (2.2):
  - Refer to the insulin infusion pump user manual to see if ADMELOG can be used. Use in accordance with the insulin pump instructions for use.
  - Administer ADMELOG by continuous subcutaneous infusion using an insulin pump in a region recommended in the instructions from the pump manufacturer.
  - Rotate infusion sites to reduce risk of lipodystrophy and localized cutaneous amyloidosis.
  - Do not mix with other insulins or diluents in the pump.
- Intravenous Infusion: Administer ADMELOG by intravenous infusion ONLY after dilution and under medical supervision. (2.2)
- The dosage of ADMELOG must be individualized based on the route of administration and the patient's metabolic needs, blood glucose monitoring results and glycemic control goal. (2.3)

3 DOSAGE FORMS AND STRENGTHS

Injection: 100 units/mL (U-100) is available as: (3)

- 3 mL single-patient-use SoloStar®prefilled pens

4 CONTRAINDICATIONS

- Do not use during episodes of hypoglycemia. (4)
- Do not use in patients with hypersensitivity to insulin lispro or any of the excipients in ADMELOG. (4)

5 WARNINGS AND PRECAUTIONS

- Never sharean ADMELOG SoloStar disposable prefilled pen or syringe between patients, even if the needle is changed. (5.1)
- Hyperglycemia or Hypoglycemia with Changes in Insulin Regimen:Make changes to a patient's insulin regimen (e.g., insulin strength, manufacturer, type, injection site or method of administration) under close medical supervision with increased frequency of blood glucose monitoring. (5.2)
- Hypoglycemia:May be life-threatening. Monitor blood glucose and increase monitoring frequency with changes to insulin dosage, use of glucose lowering medications, meal pattern, physical activity; in patients with renal or hepatic impairment; and in patients with hypoglycemia unawareness. (5.3, 6, 7, 8.6, 8.7)
- Hypoglycemia Due to Medication Errors:Accidental mix-ups between insulin products can occur. Instruct patients to check insulin labels before injection. (5.4)
- Hypersensitivity Reactions:May be life-threatening. Discontinue ADMELOG, monitor and treat if indicated. (5.5)
- Hypokalemia:May be life-threatening. Monitor potassium levels in patients at risk of hypokalemia and treat if indicated. (5.6)
- Fluid Retention and Heart Failure with Concomitant Use of Thiazolidinediones (TZDs):Observe for signs and symptoms of heart failure; consider dosage reduction or discontinuation if heart failure occurs. (5.7)
- Hyperglycemia and Ketoacidosis Due to Insulin Pump Device Malfunction:Monitor glucose and administer ADMELOG by subcutaneous injection if pump malfunction occurs. (5.8)

6 ADVERSE REACTIONS

Adverse reactions associated with ADMELOG include hypoglycemia, allergic reactions, injection site reactions, lipodystrophy, pruritus, and rash. (6.1)

To report SUSPECTED ADVERSE REACTIONS, contact sanofi-aventis at 1-800-633-1610 or FDA at 1-800-FDA-1088 or www.fda.gov/medwatch.

7 DRUG INTERACTIONS

- Drugs that may increase the risk of hypoglycemia:antidiabetic agents, ACE inhibitors, angiotensin II receptor blocking agents, disopyramide, fibrates, fluoxetine, monoamine oxidase inhibitors, pentoxifylline, pramlintide, salicylates, somatostatin analog (e.g., octreotide), and sulfonamide antibiotics (7).
- Drugs that may decrease the blood glucose lowering effect:atypical antipsychotics, corticosteroids, danazol, diuretics, estrogens, glucagon, isoniazid, niacin, oral contraceptives, phenothiazines, progestogens (e.g., in oral contraceptives), protease inhibitors, somatropin, sympathomimetic agents (e.g., albuterol, epinephrine, terbutaline), and thyroid hormones (7).
- Drugs that may increase or decrease the blood glucose lowering effect:alcohol, beta-blockers, clonidine, lithium salts, and pentamidine (7).
- Drugs that may blunt the signs and symptoms of hypoglycemia:beta-blockers, clonidine, guanethidine, and reserpine (7).

FULL PRESCRIBING INFORMATION

1 INDICATIONS AND USAGE

ADMELOG is indicated to improve glycemic control in adult and pediatric patients with diabetes mellitus.

2 DOSAGE AND ADMINISTRATION

2.1 Important Preparation and Administration Instructions

- Always check insulin labels before administration [see Warnings and Precautions (5.4)] .
- Inspect ADMELOG visually before use. It should appear clear and colorless. Do not use ADMELOG if particulate matter or coloration is seen.
- Use ADMELOG SoloStar prefilled pen with caution in patients with visual impairment who may rely on audible clicks to dial their dose.
- Do NOT mix ADMELOG with other insulins when administering using a continuous subcutaneous infusion pump.

2.2 Preparation and Administration Instructions for the Approved Routes of Administration

Subcutaneous Injection

- Administer the dose of ADMELOG subcutaneously within fifteen minutes before a meal or immediately after a meal into the abdominal wall, thigh, upper arm, or buttocks.
- Rotate injection site within the same region from one injection to the next to reduce the risk of lipodystrophy and localized cutaneous amyloidosis. Do not inject into areas of lipodystrophy or localized cutaneous amyloidosis [see Warnings and Precautions (5.2), Adverse Reactions (6)] .
- During changes to a patient's insulin regimen, increase the frequency of blood glucose monitoring [see Warnings and Precautions (5.2)] .
- ADMELOG administered by subcutaneous injection should generally be used in regimens with intermediate or long-acting insulin.
- The ADMELOG SoloStar prefilled pen dials in 1-unit increments.
- Prior to subcutaneous use, ADMELOG may be diluted with sterile 0.9% Sodium Chloride Injection. Dilute one-part ADMELOG to one-part 0.9% Sodium Chloride Injection to yield a concentration one-half that of ADMELOG (equivalent to U-50). If diluted ADMELOG is not used immediately, refrigerate at 2°C to 8°C (36°F to 46°F) for no more than 24 hours or store at room temperature up to 30°C (86°F) for 4 hours. Discard the unused diluted ADEMLOG after 24 hours if refrigerated or after 4 hours if stored at room temperature.

Continuous Subcutaneous Infusion (Insulin Pump)

- Refer to the continuous subcutaneous insulin infusion pump user manual to see if ADMELOG can be used with the insulin pump. Use ADMELOG in accordance with the insulin pump system's instructions for use.
- Administer ADMELOG by continuous subcutaneous infusion in a region recommended in the instructions from the pump manufacturer. Rotate infusion sites within the same region to reduce the risk of lipodystrophy and localized cutaneous amyloidosis. Do not inject into areas of lipodystrophy or localized cutaneous amyloidosis [see Warnings and Precautions (5.2), Adverse Reactions (6)] .
- Train patients using continuous subcutaneous insulin infusion therapy to administer insulin by injection and have alternate insulin therapy available in case of insulin pump failure [see Warnings and Precautions (5.8)].
- During changes to a patient's insulin regimen, increase the frequency of blood glucose monitoring [see Warnings and Precautions (5.2)] .
- Change ADMELOG in the pump reservoir at least every 7 days or according to the pump user manual, whichever is shorter.
- Change the infusion sets and the infusion set insertion site according to the manufacturer's user manual.
- Do NOT dilute or mix ADMELOG when administering by continuous subcutaneous infusion.
- Do NOT expose ADMELOG in the pump reservoir to temperatures greater than 98.6°F (37°C).

Intravenous Administration

- Administer ADMELOG intravenously ONLY under medical supervision [see Warnings and Precautions (5.3, 5.6)] .
- Dilute ADMELOG to concentrations from 0.1 unit/mL to 1 unit/mL using 0.9% Sodium Chloride Injection, USP [see How Supplied/Storage and Handling (16.2)] .
- Closely monitor of blood glucose and potassium levels to avoid hypoglycemia and hypokalemia [see Warnings and Precautions (5.3, 5.6)].

2.3 Dosage Recommendations

- Individualize and adjust the dosage of ADMELOG based on the route of administration, the patient's metabolic needs, blood glucose monitoring results, and glycemic control goal.
- Dosage modifications may be needed with changes in physical activity, changes in meal patterns (i.e., macronutrient content or timing of food intake), changes in renal or hepatic function, or during acute illness [see Warnings and Precautions (5.2, 5.3)and Use in Specific Populations (8.6, 8.7)] .
- When switching from another insulin lispro product to ADMELOG, the dose of ADMELOG should be the same as the other insulin lispro product [see Warnings and Precautions (5.2)].
- When switching from other insulins to ADMELOG, the ADMELOG dosage may need to be adjusted [see Warnings and Precautions (5.2)] .

2.4 Dosage Adjustment for Drug Interactions

- Dosage modification may be needed when ADMELOG is coadministered with certain drugs [see Drug Interactions (7)].
- Do NOT mix ADMELOG with any other insulin.

3 DOSAGE FORMS AND STRENGTHS

Injection: 100 units/mL (U-100) is a clear and colorless solution available as:

- 3 mL single-patient-use SoloStar prefilled pens

4 CONTRAINDICATIONS

ADMELOG is contraindicated:

- during episodes of hypoglycemia [see Warnings and Precautions (5.3)] .
- in patients who are hypersensitive to insulin lispro or to any of the excipients in ADMELOG [see Warnings and Precautions (5.5)].

5 WARNINGS AND PRECAUTIONS

5.1 Never Share an ADMELOG SoloStar Pen or Syringe Between Patients

ADMELOG SoloStar prefilled pen must never be shared between patients, even if the needle is changed. Patients using ADMELOG vials must never share needles or syringes with another person. Sharing poses a risk for transmission of blood-borne pathogens.

5.2 Hyperglycemia or Hypoglycemia with Changes in Insulin Regimen

Changes in an insulin regimen (e.g., insulin strength, manufacturer, type, injection site or method of administration) may affect glycemic control and predispose to hypoglycemia [see Warnings and Precautions (5.3)] or hyperglycemia. Repeated insulin injections into areas of lipodystrophy or localized cutaneous amyloidosis have been reported to result in hyperglycemia; and a sudden change in the injection site (to unaffected area) has been reported to result in hypoglycemia [see Adverse Reactions (6)] .

Make any changes to a patient's insulin regimen under close medical supervision with increased frequency of blood glucose monitoring. Advise patients who have repeatedly injected into areas of lipodystrophy or localized cutaneous amyloidosis to change the injection site to unaffected areas and closely monitor for hypoglycemia. For patients with type 2 diabetes, dosage adjustments of concomitant anti-diabetic products may be needed.

5.3 Hypoglycemia

Hypoglycemia is the most common adverse reaction associated with insulins, including ADMELOG.

Severe hypoglycemia can cause seizures, may be life-threatening, or cause death. Hypoglycemia can impair concentration ability and reaction time; this may place an individual and others at risk in situations where these abilities are important (e.g., driving or operating other machinery).

Hypoglycemia can happen suddenly, and symptoms may differ in each individual and change over time in the same individual. Symptomatic awareness of hypoglycemia may be less pronounced in patients with longstanding diabetes, in patients with diabetic nerve disease, in patients using medications that block the sympathetic nervous system (e.g., beta-blockers) [see Drug Interactions (7)] , or in patients who experience recurrent hypoglycemia.

Risk Factors for Hypoglycemia

The risk of hypoglycemia after an injection is related to the duration of action of the insulin and, in general, is highest when the glucose lowering effect of the insulin is maximal. As with all insulins, the glucose lowering effect time course of ADMELOG may vary in different individuals or at different times in the same individual and depends on many conditions, including the area of injection as well as the injection site blood supply and temperature [see Clinical Pharmacology (12.2)] . Other factors which may increase the risk of hypoglycemia include changes in meal pattern (e.g., macronutrient content or timing of meals), changes in level of physical activity, or changes to co-administered medication [see Drug Interactions (7)] . Patients with renal or hepatic impairment may be at higher risk of hypoglycemia [see Use in Specific Populations (8.6, 8.7)] .

Risk Mitigation Strategies for Hypoglycemia

Patients and caregivers must be educated to recognize and manage hypoglycemia. Self-monitoring of blood glucose plays an essential role in the prevention and management of hypoglycemia. In patients at higher risk for hypoglycemia and patients who have reduced symptomatic awareness of hypoglycemia, increased frequency of blood glucose monitoring is recommended.

5.4 Hypoglycemia Due to Medication Errors

Accidental mix-ups between insulin products have been reported. To avoid medication errors between ADMELOG and other insulins, instruct patients to always check the insulin label before each injection.

5.5 Hypersensitivity Reactions

Severe, life-threatening, generalized allergy, including anaphylaxis, can occur with insulins, including ADMELOG. If hypersensitivity reactions occur, discontinue ADMELOG; treat per standard of care and monitor until symptoms and signs resolve [see Adverse Reactions (6.1)] . ADMELOG is contraindicated in patients who have had hypersensitivity reactions to insulin lispro or any of the excipients in ADMELOG [see Contraindications (4)] .

5.6 Hypokalemia

All insulins, including ADMELOG, cause a shift in potassium from the extracellular to intracellular space, possibly leading to hypokalemia. Untreated hypokalemia may cause respiratory paralysis, ventricular arrhythmia, and death. Monitor potassium levels in patients at risk for hypokalemia if indicated (e.g., patients using potassium-lowering medications, patients taking medications sensitive to serum potassium concentrations).

5.7 Fluid Retention and Heart Failure with Concomitant Use of PPAR-gamma Agonists

Thiazolidinediones (TZDs), which are peroxisome proliferator-activated receptor (PPAR)-gamma agonists, can cause dose-related fluid retention, particularly when used in combination with insulin. Fluid retention may lead to or exacerbate heart failure. Patients treated with insulin, including ADMELOG, and a PPAR-gamma agonist should be observed for signs and symptoms of heart failure. If heart failure develops, it should be managed according to current standards of care, and discontinuation or dose reduction of the PPAR-gamma agonist must be considered.

5.8 Hyperglycemia and Ketoacidosis Due to Insulin Pump Device Malfunction

Malfunction of the insulin pump or insulin infusion set or insulin degradation can rapidly lead to hyperglycemia and ketoacidosis. Prompt identification and correction of the cause of hyperglycemia or ketosis is necessary. Interim subcutaneous injections with ADMELOG may be required. Patients using continuous subcutaneous insulin infusion pump therapy must be trained to administer insulin by injection and have alternate insulin therapy available in case of pump failure [see How Supplied/Storage and Handling (16.2)and Patient Counseling Information (17)] .

6 ADVERSE REACTIONS

The following adverse reactions are discussed elsewhere:

- Hypoglycemia [see Warnings and Precautions (5.3)]
- Hypoglycemia Due to Medication Errors [see Warnings and Precautions (5.4)]
- Hypersensitivity Reactions [see Warnings and Precautions (5.5)]
- Hypokalemia [see Warnings and Precautions (5.6)]

6.1 Clinical Trials Experience

Because clinical trials are conducted under widely varying conditions, adverse reaction rates observed in the clinical trials of a drug cannot be directly compared to rates in the clinical trials of another drug and may not reflect the rates observed in practice.

Adverse Reactions with Subcutaneous Injections of ADMELOG

Two clinical trials with ADMELOG were conducted: one in patients with type 1 diabetes and one in patients with type 2 diabetes [see Clinical Studies (14)] .

- The data in Table 1 reflect the exposure of 252 patients with type 1 diabetes to ADMELOG with mean exposure duration of 49 weeks. The type 1 diabetes population had the following characteristics: Mean age was 43 years and mean duration of diabetes was 20 years. Fifty-nine percent were male, 80% were White, 6% were Black or African American and 7% were Hispanic. At baseline, the mean eGFR was 90 mL/min/1.73 m^2and 49% of patients had eGFR ≥90 mL/min/1.73 m^2. The mean BMI was 26 kg/m^2. The mean HbA1c at baseline was 8.07%.
- Two hundred fifty-three patients with type 2 diabetes were exposed to ADMELOG with mean exposure duration of 25 weeks. The type 2 diabetes population had the following characteristics: Mean age was 62 years and mean duration of diabetes was 17 years. Fifty-four percent were male, 90% were White, 6% were Black or African American and 17% were Hispanic. At baseline, the mean eGFR was 77 mL/min/1.73 m^2and 27% of patients had eGFR ≥90 mL/min/1.73 m^2. The mean BMI was 32 kg/m^2. The mean HbA1c at baseline was 7.99%.

Common adverse reactions were defined as reactions that occurred in ≥5% of the population studied.

Common adverse reactions (other than hypoglycemia) during a clinical trial in patients with type 1 diabetes mellitus are listed in Table 1. In a 26-week clinical trial in patients with type 2 diabetes mellitus, no adverse reactions (other than hypoglycemia) occurred in ≥5% of ADMELOG-treated patients (n=253) were observed.

Table 1: Adverse Reactions that Occurred in ≥5% of ADMELOG-Treated Patients with Type 1 Diabetes in a 52-Week Trial
 | ADMELOG + Insulin Glargine (100 units/mL), % (n=252)
Nasopharyngitis | 13%
Upper respiratory tract infection | 6%

Severe Hypoglycemia

Hypoglycemia is the most commonly observed adverse reaction in patients using insulin, including ADMELOG [see Warnings and Precautions (5.3)] . The rates of reported hypoglycemia depend on the definition of hypoglycemia used, diabetes type, insulin dose, intensity of glucose control, background therapies, and other intrinsic and extrinsic patient factors. For these reasons, comparing rates of hypoglycemia in clinical trials for ADMELOG with the incidence of hypoglycemia for other products may be misleading and also, may not be representative of hypoglycemia rates that will occur in clinical practice.

In the ADMELOG trials, severe hypoglycemia was defined as an event requiring assistance of another person to actively administer carbohydrate, glucagon, or other resuscitative actions. The incidence of severe hypoglycemia in patients receiving ADMELOG with type 1 diabetes mellitus and type 2 diabetes mellitus was 13.5% at 52 weeks and 2.4% at 26 weeks, respectively [see Clinical Studies (14)] .

Adverse Reactions Associated with Insulin Initiation and Intensification of Glucose Control

Intensification or rapid improvement in glucose control has been associated with a transitory, reversible ophthalmologic refraction disorder, worsening of diabetic retinopathy, and acute painful peripheral neuropathy. However, long-term glycemic control decreases the risk of diabetic retinopathy and neuropathy.

Lipodystrophy

Long-term use of insulin, including ADMELOG, can cause lipodystrophy at the site of repeated insulin injections or infusion. Lipodystrophy includes lipohypertrophy (thickening of adipose tissue) and lipoatrophy (thinning of adipose tissue) and may affect insulin absorption [see Dosage and Administration (2.2)] .

Weight Gain

Weight gain can occur with insulins, including ADMELOG, and has been attributed to the anabolic effects of insulin and the decrease in glucosuria.

Peripheral Edema

Insulins, including ADMELOG, may cause sodium retention and edema, particularly if previously poor metabolic control is improved by intensified insulin therapy.

Adverse Reactions with Continuous Subcutaneous Insulin Infusion (CSII) of ADMELOG

In a randomized, open-label crossover study in adult patients with type 1 diabetes treated over two 4-week periods, the incidence of infusion set occlusions (defined as failure to correct hyperglycemia [plasma glucose ≥300 mg/dL] by insulin bolus via insulin pump) in ADMELOG-treated patients (n=25) was evaluated. Infusion set occlusions were reported by 24% of patients.

In a randomized, 16-week, open-label, parallel design study of pediatric patients with type 1 diabetes, adverse reactions related to infusion site-related reactions for another insulin lispro product, 100 units/mL, occurred in 21% of patients. The most frequently reported infusion site-related reactions were infusion site erythema and infusion site reaction.

Allergic Reactions

Local Allergy

As with any insulin therapy, patients taking ADMELOG may experience redness, swelling, or itching at the site of the injection. These minor reactions usually resolve in a few days to a few weeks, but in some occasions may require discontinuation of ADMELOG. In some instances, these reactions may be related to factors other than insulin, such as irritants in a skin cleansing agent or poor injection technique.

Systemic Allergy

Severe, life-threatening, generalized allergy, including anaphylaxis, may occur with any insulin, including ADMELOG. Generalized allergy to insulin may cause whole body rash (including pruritus), dyspnea, wheezing, hypotension, tachycardia, or diaphoresis.

Localized reactions and generalized myalgias have been reported with injected metacresol, which is an excipient in ADMELOG [see Contraindications (4)] .

6.2 Immunogenicity

As with all therapeutic proteins, there is potential for immunogenicity. The detection of antibody formation is highly dependent on the sensitivity and specificity of the assay. Additionally, the observed incidence of antibody (including neutralizing antibody) positivity in an assay may be influenced by several factors including assay methodology, sample handling, timing of sample collection, concomitant medication, and underlying disease. For these reasons, comparison of the incidence of antibodies to ADMELOG in the studies described below with the incidence of antibodies in other studies or to other insulin products may be misleading.

In a 52-week study of ADMELOG in type 1 diabetes patients, 49.4% were positive at baseline and 22.6% had treatment-emergent ADA (i.e., either new ADA, or increase in titer of at least 4-fold).

In a 26-week study of ADMELOG in type 2 diabetes patients, 26.4% were positive at baseline and 18.8% had treatment-emergent ADA (i.e., either new ADA, or increase in titer of at least 4-fold).

6.3 Postmarketing Experience

The following additional adverse reactions have been identified during post approval use of another insulin lispro product, 100 units/mL. Because these reactions are reported voluntarily from a population of uncertain size, it is not always possible to reliably estimate their frequency or establish a causal relationship to drug exposure.

Medication errors in which other insulins have been accidentally substituted for another insulin lispro product, 100 units/mL, have been identified during post approval use.

Localized cutaneous amyloidosis at the injection site has occurred. Hyperglycemia has been reported with repeated insulin injections into areas of localized cutaneous amyloidosis; hypoglycemia has been reported with a sudden change to an unaffected injection site.

7 DRUG INTERACTIONS

Table 2 presents clinically significant drug interactions with ADMELOG.

Table 2: Clinically Significant Drug Interactions with ADMELOG
Drugs That May Increase the Risk of Hypoglycemia
Drugs: | Antidiabetic agents, ACE inhibitors, angiotensin II receptor blocking agents, disopyramide, fibrates, fluoxetine, monoamine oxidase inhibitors, pentoxifylline, pramlintide, salicylates, somatostatin analogs (e.g., octreotide), and sulfonamide antibiotics.
Intervention: | Dose adjustment and increased frequency of glucose monitoring may be required when ADMELOG is concomitantly administered with these drugs.
Drugs That May Decrease the Blood Glucose Lowering Effect of ADMELOG
Drugs: | Atypical antipsychotics (e.g., olanzapine and clozapine), corticosteroids, danazol, diuretics, estrogens, glucagon, isoniazid, niacin, oral contraceptives, phenothiazines, progestogens (e.g., in oral contraceptives), protease inhibitors, somatropin, sympathomimetic agents (e.g., albuterol, epinephrine, terbutaline), and thyroid hormones.
Intervention: | Dose adjustment and increased frequency of glucose monitoring may be required when ADMELOG is concomitantly administered with these drugs.
Drugs That May Increase or Decrease the Blood Glucose Lowering Effect of ADMELOG
Drugs: | Alcohol, beta-blockers, clonidine, and lithium salts. Pentamidine may cause hypoglycemia, which may sometimes be followed by hyperglycemia.
Intervention: | Dose adjustment and increased frequency of glucose monitoring may be required when ADMELOG is concomitantly administered with these drugs.
Drugs That May Blunt Signs and Symptoms of Hypoglycemia
Drugs: | Beta-blockers, clonidine, guanethidine and reserpine.
Intervention: | Increased frequency of glucose monitoring may be required when ADMELOG is concomitantly administered with these drugs.

8 USE IN SPECIFIC POPULATIONS

8.1 Pregnancy

Risk Summary

Published studies with another insulin lispro product used during pregnancy have not reported an association between insulin lispro and the induction of major birth defects, miscarriage, or adverse maternal or fetal outcomes [see Data] . There are risks to the mother and fetus associated with poorly controlled diabetes in pregnancy [see Clinical Considerations] .

Pregnant rats and rabbits were exposed to another insulin lispro product in animal reproduction studies during organogenesis. Fetal growth retardation was observed in offspring of rats exposed to insulin lispro at a dose approximately 3 times the human subcutaneous dose of 1.0 unit/kg/day. No adverse effects on embryo-fetal development were observed in offspring of rabbits exposed to insulin lispro at doses up to approximately 0.24 times the human subcutaneous dose of 1.0 unit/kg/day [see Data] .

The estimated background risk of major birth defects is 6%–10% in women with pregestational diabetes with a HbA1c >7% and has been reported to be as high as 20%–25% in women with a HbA1c >10%. The estimated background risk of miscarriage for the indicated population is unknown. In the U.S. general population, the estimated background risk of major birth defects and miscarriage in clinically recognized pregnancies is 2%–4% and 15%–20%, respectively.

Clinical Considerations

Disease-associated maternal and/or embryo-fetal risk

Poorly controlled diabetes in pregnancy increases the maternal risk for diabetic ketoacidosis, preeclampsia, spontaneous abortions, preterm delivery, and delivery complications. Poorly controlled diabetes increases the fetal risk for major birth defects, stillbirth, and macrosomia related morbidity.

Data

Human data

Published data from retrospective studies and meta-analyses do not report an association with another insulin lispro product and major birth defects, miscarriage, or adverse maternal or fetal outcomes when insulin lispro is used during pregnancy. However, these studies cannot definitely establish or exclude the absence of any risk because of methodological limitations including small sample size, selection bias, confounding by unmeasured factors, and some lacking comparator groups.

Animal data

In a combined fertility and embryo-fetal development study with another insulin lispro product, female rats were given subcutaneous insulin lispro injections of 5 and 20 units/kg/day (0.8 and 3 times the human subcutaneous dose of 1 unit/kg/day, based on units/body surface area, respectively) from 2 weeks prior to cohabitation through Gestation Day 19. There were no adverse effects on female fertility, implantation, or fetal viability and morphology. However, fetal growth retardation was observed at the 20 units/kg/day dose as indicated by decreased fetal weight and an increased incidence of fetal runts/litter.

In an embryo-fetal development study in pregnant rabbits with another insulin lispro product, insulin lispro doses of 0.1, 0.25, and 0.75 unit/kg/day (0.03, 0.08, and 0.24 times the human subcutaneous dose of 1 unit/kg/day, based on units/body surface area, respectively) were injected subcutaneously on Gestation Days 7 through 19. There were no adverse effects on fetal viability, weight, and morphology at any dose.

8.2 Lactation

Risk Summary

Available data from published literature suggest that exogenous human insulin products, including insulin lispro, are transferred into human milk. There are no adverse reactions reported in breastfed infants in the literature. There are no data on the effects of exogenous human insulin products, including insulin lispro, on milk production. The developmental and health benefits of breastfeeding should be considered along with the mother's clinical need for ADMELOG and any potential adverse effects on the breastfed child from ADMELOG or from the underlying maternal condition.

8.4 Pediatric Use

The safety and effectiveness of ADMELOG to improve glycemic control have been established in pediatric patients with diabetes mellitus. Use of ADMELOG for this indication is supported by evidence from an adequate and well-controlled study with another insulin lispro product, 100 units/ml, in 60 pediatric patients 3 years of age and older with type 1 diabetes mellitus and studies in adult patients with diabetes mellitus [see Clinical Studies (14)] .

8.5 Geriatric Use

Of the total number of patients (n=2,834) in eight clinical studies of another insulin lispro product, 100 units/mL, 12% (n=338) were 65 years of age or over. The majority of these patients had type 2 diabetes. HbA1c values and hypoglycemia rates did not differ by age.

Of the total number of patients (n=1,011) in clinical studies of ADMELOG or another insulin lispro product, 100 units/mL, 26.5% (n=268) were 65 years of age or over. The majority of these patients had type 2 diabetes. HbA1c values and hypoglycemia rates did not differ by age.

Pharmacokinetic/pharmacodynamic studies to assess the effect of age on the onset of ADMELOG action have not been performed.

8.6 Renal Impairment

Patients with renal impairment may be at increased risk of hypoglycemia and may require more frequent ADMELOG dose adjustment and more frequent blood glucose monitoring [see Clinical Pharmacology (12.3)] .

8.7 Hepatic Impairment

Patients with hepatic impairment may be at increased risk of hypoglycemia and may require more frequent ADMELOG dose adjustment and more frequent blood glucose monitoring [see Clinical Pharmacology (12.3)] .

10 OVERDOSAGE

Excess insulin administration may cause hypoglycemia and hypokalemia. Mild episodes of hypoglycemia usually can be treated with oral glucose. Adjustments in drug dosage, meal patterns, or exercise may be needed. More severe episodes with coma, seizure, or neurologic impairment may be treated with a glucagon product for emergency use or concentrated intravenous glucose. Sustained carbohydrate intake and observation may be necessary because hypoglycemia may recur after apparent clinical recovery. Hypokalemia must be corrected appropriately.

11 DESCRIPTION

Insulin lispro is a rapid-acting human insulin analog produced by recombinant DNA technology utilizing a non-pathogenic laboratory strain of Escherichia coli. Insulin lispro differs from human insulin in that the amino acid proline at position B28 is replaced by lysine and the lysine in position B29 is replaced by proline. Insulin lispro has a molecular weight of 5808 Da, identical to that of human insulin.

ADMELOG (insulin lispro) injection is a sterile, aqueous, clear, and colorless solution for subcutaneous or intravenous use. Each mL of ADMELOG contains 100 units of insulin lispro, and the inactive ingredients: dibasic sodium phosphate (1.88 mg), glycerin (16 mg), metacresol (3.15 mg), zinc oxide (content adjusted to provide 0.0197 mg zinc ion), and Water for Injection, USP. Insulin lispro has a pH of 7.0 to 7.8. The pH is adjusted by addition of aqueous solutions of hydrochloric acid and/or sodium hydroxide. ADMELOG is latex free.

12 CLINICAL PHARMACOLOGY

12.1 Mechanism of Action

Regulation of glucose metabolism is the primary activity of insulins and insulin analogs, including insulin lispro products. Insulins lower blood glucose by stimulating peripheral glucose uptake by skeletal muscle and fat, and by inhibiting hepatic glucose production. Insulins inhibit lipolysis and proteolysis and enhance protein synthesis.

12.2 Pharmacodynamics

Pharmacodynamics of ADMELOG After Subcutaneous Injection

The pharmacodynamic profile of a single 0.3 unit/kg dose of ADMELOG administered subcutaneously was evaluated in a euglycemic clamp study enrolling 30 patients with type 1 diabetes. In this study, the mean (SD) time to maximum effect of ADMELOG (measured by the peak rate of glucose infusion) was approximately 2.1 (0.8) hours. The mean (SD) area under the glucose infusion rate curves (measure of overall pharmacodynamic effect) and mean (SD) maximum glucose infusion rate were 1953.5 (547.3) mg/kg and 9.97 (2.37) mg/min/kg, respectively (see Figure 1).

Figure 1: Mean Smoothed Glucose Infusion Rate [Body Weight Standardized] after Subcutaneous Injection of ADMELOG (0.3 unit/kg) in Patients with Type 1 Diabetes

The time course of action of insulin and insulin analogs, including insulin lispro products, may vary considerably in different individuals or within the same individual. The rate of insulin absorption and, consequently, the onset of activity are known to be affected by the site of injection, exercise, and other variables [see Warnings and Precautions (5.2)] .

Pharmacodynamics of AMELOG after Intravenous Administration

The glucose lowering effect of intravenous administration of another insulin lispro product, 100 units/mL, was tested in 21 patients with type 1 diabetes. For the study, the patients' usual doses of insulin were held, and blood glucose concentrations were allowed to reach a stable range of 200 to 260 mg/dL during a one to three-hour run-in phase. The run-in phase was followed by a 6-hour assessment phase. During the assessment phase, patients received intravenous infusion of another insulin lispro product, 100 units/mL, at an initial infusion rate of 0.5 units/hour. The infusion rate could be adjusted at regular timed intervals to achieve and maintain blood glucose concentrations between 100 to 160 mg/dL.

The mean blood glucose levels during the assessment phase for patients on another insulin lispro product, 100 units/mL, therapy are summarized below in Table 3. All patients achieved the targeted glucose range at some point during the 6-hour assessment phase. At the endpoint, blood glucose was within the target range (100 to 160 mg/dL) for 17 of 20 patients treated with another insulin lispro product, 100 units/mL. The average time (±SE) required to attain near normoglycemia was 129 ± 14 minutes for another insulin lispro product, 100 units/mL.

Table 3: Mean Blood Glucose Concentrations (mg/dL) During Intravenous Infusions of Another Insulin Lispro Product, 100 units/mL in Patients with Type 1 Diabetes
Time from Start of Infusion (minutes) | Mean Blood Glucose (mg/dL) Intravenous [Results shown as mean ± SD.]
0 | 224 ± 16
30 | 205 ± 21
60 | 195 ± 20
120 | 165 ± 26
180 | 140 ± 26
240 | 123 ± 20
300 | 120 ± 27
360 | 122 ± 25

12.3 Pharmacokinetics

Absorption

The pharmacokinetic profile of a single 0.3 unit/kg dose of ADMELOG administered subcutaneously was evaluated in a study enrolling 30 patients with type 1 diabetes. In this study, the mean observed area under the plasma insulin lispro concentration-time curve from time zero to infinity and peak plasma insulin lispro concentration were 12800 pg∙hr/mL and 5070 pg/mL, respectively. The median time to maximum plasma insulin lispro concentration was 0.83 hours after injection (see Figure 2).

Figure 2: Mean Plasma Concentrations of ADMELOG after a Single Subcutaneous Administration of ADMELOG (0.3 unit/kg) in Patients with Type 1 Diabetes

The absolute bioavailability of another insulin lispro product, 100 units/mL, after subcutaneous injection ranges from 55% to 77% with doses between 0.1 to 0.2 unit/kg, inclusive.

Distribution

When administered intravenously as bolus injections of 0.1 and 0.2 unit/kg dose in two separate groups of healthy subjects, the mean volume of distribution of another insulin lispro product, 100 units/mL, appeared to decrease with increase in dose (1.55 and 0.72 L/kg, respectively).

Elimination

Metabolism

Human metabolism studies have not been conducted. However, animal studies indicate that the metabolism of another insulin lispro product, 100 units/mL, is identical to that of regular human insulin.

Excretion

When administered intravenously, another insulin lispro product, 100 units/mL demonstrated dose-dependent clearance, with a mean clearance of 21.0 mL/min/kg (0.1 unit/kg dose), and 9.6 mL/min/kg (0.2 unit/kg dose). Another insulin lispro product, 100 units/mL, demonstrated a mean t1/2of 0.85 hours (51 minutes) and 0.92 hours (55 minutes), respectively for 0.1 unit/kg and 0.2 unit/kg doses.

Specific Populations

The effects of age, gender, race, obesity, pregnancy, or smoking on the pharmacokinetics of ADMELOG have not been studied.

Patients with Renal Impairment

Type 2 diabetic patients with varying degrees of renal impairment showed no difference in pharmacokinetics of another insulin lispro product, 100 units/mL. However, the sensitivity of the patients to insulin did change, with an increased response to insulin as the renal function declined. Some studies with human insulin have shown increased circulating levels of insulin in patients with renal impairment [see Use in Specific Populations (8.6)] .

Patients with Hepatic Impairment

Type 2 diabetic patients with impaired hepatic function showed no effect on the pharmacokinetics of another insulin lispro product, 100 units/mL, as compared to patients with no hepatic dysfunction. However, some studies with human insulin have shown increased circulating levels of insulin in patients with liver failure [see Use in Specific Populations (8.7)] .

13 NONCLINICAL TOXICOLOGY

13.1 Carcinogenesis, Mutagenesis, Impairment of Fertility

Standard 2-year carcinogenicity studies in animals have not been performed. In Fischer 344 rats, a 12-month repeat-dose toxicity study was conducted with insulin lispro at subcutaneous doses of 20 and 200 units/kg/day (approximately 3 and 32 times the human subcutaneous dose of 1 unit/kg/day, based on units/body surface area). Insulin lispro did not produce important target organ toxicity including mammary tumors at any dose.

Insulin lispro was not mutagenic in the following genetic toxicity assays: bacterial mutation, unscheduled DNA synthesis, mouse lymphoma, chromosomal aberration, and micronucleus assays.

Male fertility was not compromised when male rats given subcutaneous insulin lispro injections of 5 and 20 units/kg/day (0.8 and 3 times the human subcutaneous dose of 1 unit/kg/day, based on units/body surface area) for 6 months were mated with untreated female rats. In a combined fertility, perinatal, and postnatal study in male and female rats given 1, 5, and 20 units/kg/day subcutaneously (0.16, 0.8, and 3 times the human subcutaneous dose of 1 unit/kg/day, based on units/body surface area), mating and fertility were not adversely affected in either gender at any dose.

14 CLINICAL STUDIES

14.1 Overview of Clinical Studies

The safety and effectiveness of ADMELOG to improve glycemic control in adult and pediatric patients with diabetes mellitus have been established based on adequate and well-controlled studies of ADMELOG in adult patients with type 1 and type 2 diabetes mellitus, and based on adequate and well-controlled studies of another insulin lispro product, 100 units/mL, in adult and pediatric patients 3 years of age and older with type 1 diabetes mellitus and adult patients with type 2 diabetes mellitus.

The safety and effectiveness of:

- ADMELOG were studied in 507 adult patients with type 1 diabetes and 505 adult patients with type 2 diabetes.
- Another insulin lispro product, 100 units/mL, were studied in 1,087 adult and pediatric patients with type 1 diabetes and in 722 adult patients with type 2 diabetes.

14.2 Type 1 Diabetes Mellitus – Subcutaneous Injection

ADMELOG: Study in Adult Patients

A 26-week open-label, active-controlled study (NCT02273180) evaluated the glucose lowering effect of ADMELOG plus insulin glargine, 100 units/mL, compared to that of Comparator (another insulin lispro product, 100 units/mL, or a non–U.S.-licensed insulin lispro product, 100 units/mL), plus insulin glargine, 100 units/mL. A total of 507 patients with type 1 diabetes mellitus treated with insulin glargine 100 units/mL and rapid-acting mealtime insulin analogs participated in the study. Patients were randomized to ADMELOG (n=253) or Comparator (n=254). ADMELOG or Comparator was administered by subcutaneous injection immediately prior to meals.

The mean age of these patients was 43 years old, and 60% were male. The population was 82% White, 5% Black or African American and 5% were Hispanic. The population had type 1 diabetes mellitus for a mean duration of 19 years. The mean eGFR was 90.6 mL/min/1.73 m^2and 48.7% of patients had GFR ≥90 mL/min/1.73 m^2. The mean BMI was approximately 26 kg/m^2. At baseline, 61%, 38% and 2% of the patients were using other insulin lispro products, 100 units/mL, insulin aspart, 100 units/mL, or both, respectively.

At week 26, treatment with ADMELOG provided a mean reduction in HbA1c that was non-inferior to that achieved with the Comparator (see Table 4).

Table 4: 26 Week Type 1 Diabetes Mellitus Trial in Adults – Mean Change in HbA1c (ADMELOG plus Insulin Glargine, 100 units/mL, versus Comparator plus Insulin Glargine, 100 units/mL)
 | ADMELOG + Insulin Glargine | Comparator + Insulin Glargine
N [ITT: Intent-to-treat; all randomized patients.] | 253 | 254
HbA1c (%)
Baseline (mean) | 8.08 | 7.99
Adjusted mean change from baseline [Estimated using a multiple imputation method that models a "return to baseline" for patients having missing data who discontinued treatment. ANCOVA was used with treatment and stratification groups as fixed factors and baseline HbA1c as a covariate.] | -0.40 | -0.46
Adjusted mean difference [Treatment difference: ADMELOG - Comparator.] (95% CI) | 0.06 (-0.086 to 0.201)

Another Insulin Lispro Product, 100 units/mL: Study in Adult and Pediatric Patients 12 Years of Age and Older

A 12-month, randomized, parallel, open-label, active-controlled study was conducted in 167 patients with type 1 diabetes to assess the safety and efficacy of another insulin lispro product, 100 units/mL (n=81), compared with regular human insulin, 100 units/mL (n=86). This other insulin lispro product was administered by subcutaneous injection immediately prior to meals and regular human insulin was administered 30 to 45 minutes before meals. Human insulin extended zinc suspension was administered once or twice daily as the basal insulin in both treatment groups. There was a 2 to 4-week run-in period with regular human insulin and human insulin extended zinc suspension before randomization.

The mean age of these patients was 31 years (range 12 to 70 years), and 47% were male. The population was 97% White.

Table 5: 12 Month Type 1 Diabetes Mellitus Trial in Adults and Pediatric Patients 12 Years of Age and Older – Mean Change in HbA1c% (another insulin lispro product, 100 units/mL, versus regular human insulin, 100 units/mL)
 | Another Insulin Lispro Product + Human Insulin Extended Zinc | Regular Human Insulin + Human Insulin Extended Zinc
N | 81 | 86
Baseline HbA1c (%) [Values are Mean ± SD.] | 8.2 ± 1.4 | 8.3 ± 1.7
Change from baseline HbA1c (%) | -0.1 ± 0.9 | 0.1 ± 1.1
Treatment difference in HbA1c mean (95% confidence interval) | 0.4 (0.0; 0.8)

Another Insulin Lispro Product, 100 units/mL: Studies in Pediatric Patients 3 Years of Age and Older

An 8-month, crossover study of pediatric patients with type 1 diabetes (n=463), aged 9 to 19 years, compared two subcutaneous multiple-dose treatment regimens: another insulin lispro product, 100 units/mL, or regular human insulin, 100 units/mL, both administered with NPH human insulin isophane suspension as the basal insulin. Insulin lispro achieved glycemic control comparable to regular human insulin, as measured by HbA1c (see Table 6).

Table 6: Type 1 Diabetes Mellitus Trial in Pediatric Patients 9 Years of Age and Older – Mean Change in HbA1c (%) (another insulin lispro product, 100 units/mL, versus regular human insulin, 100 units/mL)
 | Baseline | Another Insulin Lispro Product + NPH | Regular Human Insulin + NPH
HbA1c (%) [Values are Mean ± SD.] | 8.6 ± 1.5 | 8.7 ± 1.5 | 8.7 ± 1.6
Change from baseline HbA1c (%) | - | 0.1 ± 1.1 | 0.1 ± 1.3

In a 9-month, crossover study of pediatric patients with type 1 diabetes mellitus (n=60), aged 3 to 11 years, compared three subcutaneous injection regimens: another insulin lispro product, 100 units/mL, administered immediately before meals, this same insulin lispro product, 100 units/mL, administered immediately after meals and regular human insulin, 100 units/mL administered 30 minutes before meals resulted in similar glycemic control, as measured by HbA1c, regardless of treatment group.

14.3 Type 1 Diabetes Mellitus – Continuous Subcutaneous Infusion

Another Insulin Lispro Product, 100 units/mL: Studies in Adult and Pediatric Patients 15 Years of Age and Older

To evaluate the administration of another insulin lispro product, 100 units/mL, as a subcutaneous infusion via external insulin pumps, two open-label, crossover studies were performed in patients with type 1 diabetes mellitus.

- One study involved 39 patients, ages 19 to 58 years, treated for 24 weeks with another insulin lispro product, 100 units/mL, or regular human insulin 100 units/mL. After 12 weeks of treatment, the mean HbA1c values decreased from 7.8% to 7.2% in patients treated with another insulin lispro, and from 7.8% to 7.5% in the regular human insulin-treated patients.
- Another study involved 60 patients (mean age 39, range 15 to 58 years) treated for 24 weeks with either another insulin lispro product, 100 units/mL, or buffered regular human insulin, 100 units/mL. After 12 weeks of treatment, the mean HbA1c values decreased from 7.7% to 7.4% in patients treated with insulin lispro and remained unchanged from 7.7% in the buffered regular human insulin-treated patients.

Another Insulin Lispro Product, 100 units/mL: Study in Pediatric Patients 4 Years of Age and Older

A randomized, 16-week, open-label, parallel design, study of pediatric patients with type 1 diabetes mellitus (n=298), aged 4 to 18 years, compared two subcutaneous continuous infusion regimens administered via an external insulin pump: insulin aspart, 100 units/mL (n=198), or another insulin lispro product, 100 units/mL (n=100). These two treatments resulted in comparable changes from baseline in HbA1c after 16 weeks of treatment (see Table 7).

Table 7: 16 Week Type 1 Diabetes Mellitus Trial in Pediatric Patients 4 Years of Age and Older – Mean Change in HbA1c (%) (another insulin lispro product, 100 units/mL, versus insulin aspart, 100 units/mL) in Insulin Pump Study
 | Another Insulin Lispro Product | Insulin Aspart
N | 100 | 198
Baseline HbA1c (%) [Values are Mean ± SD.] | 8.2 ± 0.8 | 8.0 ± 0.9
Change from Baseline HbA1c (%) | -0.1 ± 0.7 | -0.1 ± 0.8
Treatment Difference in HbA1c, Mean (95% confidence interval) | 0.1 (-0.3, 0.1)

14.4 Type 2 Diabetes Mellitus

ADMELOG: Study in Adult Patients

A 26-week open-label, active-controlled study (NCT02294474) evaluated the glucose lowering effect of ADMELOG plus insulin glargine, 100 units/mL, compared to that of Comparator (another insulin lispro product, 100 units/mL, or a non–U.S.-licensed insulin lispro, 100 units/mL) plus insulin glargine, 100 units/mL. A total of 505 patients with type 2 diabetes mellitus treated with insulin glargine, 100 units/mL, and rapid-acting mealtime insulin analogs participated in the study. Patients were randomized to ADMELOG, 100 units/mL (n=253) or Comparator (n=252). ADMELOG or Comparator, was administered by subcutaneous injection immediately prior to meals.

The mean age of these patients was 63 years, and 53% were male. The population was 88% White, 6% Black or African American and 18% were Hispanic. The population had type 2 diabetes mellitus for a mean duration of 17 years. The mean eGFR was 77.9 mL/min/1.73 m^2and 26.9% of patients had GFR >90 mL/min/1.73 m^2. The mean BMI was approximately 32.2 kg/m^2. At baseline, 51%, 48%, and 0.4% of the patients were using other insulin lispro products, 100 units/mL, insulin aspart, 100 units/mL, or both, respectively.

At week 26, treatment with ADMELOG provided a mean reduction in HbA1c that was non-inferior to that achieved with the Comparator (see Table 8).

Table 8: 26 Week Type 2 Diabetes Mellitus Trial in Adults – Mean Change in HbA1c (%) (ADMELOG plus insulin glargine, 100 units/mL, versus Comparator plus insulin glargine, 100 units/mL)
 | ADMELOG + Insulin Glargine | Comparator + Insulin Glargine
N [ITT: Intent-to-treat; all randomized patients.] | 253 | 252
HbA1c (%)
Baseline (mean) | 8.00 | 8.03
Adjusted mean change from baseline [Estimated using a multiple imputation method that models a "return-to-baseline" for patients having missing data who discontinued treatment. ANCOVA was used with treatment and stratification groups as fixed factors and baseline HbA1c as a covariate.] | -0.86 | -0.80
Adjusted mean difference [Treatment difference: ADMELOG – Comparator.] (95% CI) | -0.06 (-0.209 to 0.091)

Another Insulin Lispro Product, 100 units/mL: Study in Adult Patients

A 6-month randomized, crossover, open-label, active-controlled study was conducted in 722 patients with type 2 diabetes mellitus treated with insulin to assess the safety and efficacy of another insulin lispro product, 100 units/mL, for 3 months followed by regular human insulin, 100 units/mL, for 3 months or the reverse sequence. This other insulin lispro product was administered by subcutaneous injection immediately before meals and regular human insulin was administered 30 to 45 minutes before meals. NPH human insulin isophane suspension or human insulin extended zinc suspension was administered once or twice daily as the basal insulin in both treatment groups. All patients participated in a 2 to 4-week run-in period with regular human insulin and NPH human insulin isophane suspension or human insulin extended zinc suspension.

Most of the patients were White (88%), and the numbers of males and females in each group were approximately equal. The mean age was 59 years (range 24 to 85 years). The average body mass index (BMI) was 28.2 kg/m^2. During the study, the majority of patients used NPH human insulin isophane suspension (84%) compared with human insulin extended zinc suspension (16%) as their basal insulin. The reductions from baseline in HbA1c were similar between the two treatments from the combined groups (see Table 9).

Table 9: 3 Month Trial in Adults with Type 2 Diabetes Mellitus– Mean Change in HbA1c (%) (another insulin lispro product, 100 units/mL, versus regular human insulin, 100 units/mL)
 | Baseline | Another Insulin Lispro Product + Basal Insulin | Regular Human Insulin + Basal Insulin
HbA1c (%) [Values are Mean ± SD.] | 8.9 ± 1.7 | 8.2 ± 1.3 | 8.2 ± 1.4
Change from baseline HbA1c (%) | - | -0.7 ± 1.4 | -0.7 ± 1.3

16 HOW SUPPLIED/STORAGE AND HANDLING

ADMELOG (insulin lispro) injection 100 units/mL (U-100) is available as a clear and colorless solution in:

3 mL single-patient-use SoloStar prefilled pen

NDC: 70518-4275-00

PACKAGING: 5 in 1 CARTON, 3 mL Syringe type 2

Each prefilled SoloStar pen is for use by a single patient.

The ADMELOG SoloStar prefilled pen dials in 1-unit increments.

16.2 Storage and Handling

Dispense in the original sealed carton with the enclosed Instructions for Use.

Store ADMELOG according to the table below. Do not freeze and do not use ADMELOG if it has been frozen. Protect from direct heat and light.

In-use (opened) ADMELOG vials and ADMELOG SoloStar pens must be used within 28 days or be discarded, even if they still contain ADMELOG.

Use in an External Insulin Pump

Change the ADMELOG in the pump reservoir at least every 7 days or according to the pump user manual, whichever is shorter, or after exposure to temperatures that exceed 98.6°F (37°C).

Diluted ADMELOG for Subcutaneous Injection

Diluted ADMELOG may remain in patient use for up to 24 hours when stored in a refrigerator (36°F–46°F [2°C–8°C]) or for up to 4 hours when stored at room temperature (86°F [30°C]). Do not dilute ADMELOG used in an external insulin pump.

Admixture for Intravenous Administration

Infusion bags prepared with ADMELOG are stable when stored in a refrigerator (36°F–46°F [2°C–8°C]) for 24 hours or may be used at room temperature for up to 4 hours [see Dosage and Administration (2.2)].

Repackaged and Distributed By:

Remedy Repack, Inc.

625 Kolter Dr. Suite #4 Indiana, PA 1-724-465-8762

17 PATIENT COUNSELING INFORMATION

Advise the patient to read the FDA-approved patient labeling (Patient Information and Instructions for Use).

Repackaged By / Distributed By: RemedyRepack Inc.

625 Kolter Drive, Indiana, PA 15701

(724) 465-8762

Never Share an ADMELOG SoloStar Prefilled Pen or Syringe Between Patients

Advise patients that they must never share an ADMELOG SoloStar pen with another person, even if the needle is changed. Advise patients using ADMELOG vials not to share needles or syringes with another person. Sharing poses a risk for transmission of blood-borne pathogens [see Warnings and Precautions (5.1)] .

Hyperglycemia or Hypoglycemia

Instruct patients on self-management procedures including glucose monitoring, proper injection technique, and management of hypoglycemia and hyperglycemia, especially at initiation of ADMELOG therapy. Instruct patients on handling of special situations such as intercurrent conditions (illness, stress, or emotional disturbances), an inadequate or skipped insulin dose, inadvertent administration of an increased insulin dose, inadequate food intake, and skipped meals. Instruct patients on the management of hypoglycemia.

Inform patients that their ability to concentrate and react may be impaired as a result of hypoglycemia. Advise patients who have frequent hypoglycemia or reduced or absent warning signs of hypoglycemia to use caution when driving or operating machinery [see Warnings and Precautions (5.3)] .

Advise patients that changes in insulin regimen can predispose to hyperglycemia or hypoglycemia and that changes in insulin regimen should be made under close medical supervision [see Warnings and Precautions (5.2)] .

Hypoglycemia due to Medication Errors

Instruct patients to always check the insulin label before each injection to avoid mix-ups between insulin products [see Warnings and Precautions (5.4)].

Hypersensitivity Reactions

Advise patients that hypersensitivity reactions have occurred with ADMELOG. Inform patients on the symptoms of hypersensitivity reactions [see Warnings and Precautions (5.5)] .

Instructions for Patients Using Continuous Subcutaneous Insulin Pumps

- Train patients in intensive insulin therapy with multiple injections and in the function of their pump and pump accessories.
- Instruct patients to follow healthcare provider recommendations when setting pump basal rates and bolus settings.
- Refer to the continuous subcutaneous infusion pump user manual to see if ADMELOG can be used with the pump. See recommended reservoir and infusion sets in the insulin pump user manual.
- Instruct patients to replace insulin in the reservoir at least every 7 days, or according to the pump user manual, whichever is shorter. By following this schedule, patients avoid insulin degradation, infusion set occlusion, and loss of the insulin preservative.
- Instruct patients that infusion sets and infusion set insertion sites should be changed according to the manufacturer's user manual.
- Instruct patients to discard insulin exposed to temperatures higher than 98.6°F (37°C). The temperature of the insulin may exceed ambient temperature when the pump housing, cover, tubing, or sport case is exposed to sunlight or radiant heat.
- Instruct patients to inform healthcare provider and select a new site for infusion if infusion site becomes erythematous, pruritic, or thickened.
- Instruct patients on the risk of rapid hyperglycemia and ketosis due to pump malfunction, infusion set occlusion, leakage, disconnection or kinking, and degraded insulin. Instruct patients on the risk of hypoglycemia from pump malfunction. If these problems cannot be promptly corrected, instruct patients to resume therapy with subcutaneous insulin injection and contact their healthcare provider [see Warnings and Precautions (5)and How Supplied/Storage and Handling (16.2)].

ADMELOG and SoloStar are registered trademarks of sanofi-aventis U.S. LLC.

©2025 sanofi-aventis U.S. LLC.

Repackaged and Distributed By:

Remedy Repack, Inc.

625 Kolter Dr. Suite #4 Indiana, PA 1-724-465-8762

PATIENT INFORMATION
ADMELOG®(ad-mah-log)
(insulin lispro)
injection, for subcutaneous or intravenous use
100 units/mL (U-100)

Do not share your ADMELOG SoloStar®Pen or syringe with other people, even if the needle has been changed. You may give other people a serious infection, or get a serious infection from them.

What is ADMELOG?

- ADMELOG is a man-made fast-acting insulin used to control high blood sugar in adults and children with diabetes mellitus.

Do not use ADMELOG if you:

- are having an episode of low blood sugar (hypoglycemia).
- have an allergy to ADMELOG or any of the ingredients in ADMELOG. See the end of this Patient Information leaflet for a complete list of ingredients in ADMELOG.

Before using ADMELOG, tell your healthcare provider about all of your medical conditions, including if you:

- have liver or kidney problems.
- take other medicines, especially ones commonly called TZDs (thiazolidinediones).
- have heart failure or other heart problems. If you have heart failure, it may get worse while you take TZDs with ADMELOG.
- are pregnant, or plan to become pregnant. Talk with your healthcare provider about the best way to control your blood sugar if you plan to become pregnant or while you are pregnant.
- are breastfeeding or plan to breastfeed. Talk to your healthcare provider about the best way to feed your baby while using ADMELOG.

Tell your healthcare provider about all the medicines you take, including prescription and over-the-counter medicines, vitamins, and herbal supplements.
Before you start using ADMELOG, talk to your healthcare provider about low blood sugar and how to manage it.

How should I use ADMELOG?

- Read the detailed Instructions for Usethat come with your ADMELOG.
- Use ADMELOG exactly as your healthcare provider tells you to. Your healthcare provider should tell you how much ADMELOG to use and when to use it.
- Know the type, strength, and amount of insulin you use. Do notchange the type or amount of insulin you use unless your healthcare provider tells you to. The amount of insulin and the best time for you to take your insulin may need to change if you take a different type of insulin.
- Check your insulin label each time you give your injection to make sure you are using the correct insulin.
- ADMELOG comes in a vial or in a SoloStar single-patient-use prefilled pen.
  Do not reuse needles. Always use a new needle for each injection. Reuse of needles increases your risk of having blocked needles, which may cause you to get the wrong dose of ADMELOG. Using a new needle for each injection also lowers your risk of getting an infection. If your needle is blocked, follow the instructions in Step 3 of the Instructions for Use of your pen.
- ADMELOG starts acting fast. Inject ADMELOG within 15 minutes before eating or right after eating a meal.
- Inject ADMELOG under the skin (subcutaneously) of your upper arms, thighs, buttocks, or stomach area (abdomen), or by continuous infusion under the skin (subcutaneously) through an insulin pump into an area of your body recommended in the instructions that come with your insulin pump.
- Change (rotate) your injection site within the area you choose with each doseto reduce your risk of getting pits in skin or thickened skin (lipodystrophy) and skin with lumps (localized cutaneous amyloidosis) at the injection sites.
  - Do notuse the exact same spot for each injection.
  - Do notinject where the skin has pits, is thickened, or has lumps.
  - Do notinject where the skin is tender, bruised, scaly or hard, or into scars or damaged skin.
- Check your blood sugar levels.Ask your healthcare provider what your blood sugar should be and when you should check your blood sugar levels.

Keep ADMELOG and all medicines out of the reach of children.

Your dose of ADMELOG may need to change because of:

- a change in physical activity or exercise, weight gain or loss, increased stress, illness, change in diet, or because of other medicines you take.

What should I avoid while using ADMELOG?
While using ADMELOG do not:

- drive or operate heavy machinery, until you know how ADMELOG affects you.
- drink alcohol or use prescription or over-the-counter medicines that contain alcohol.

What are the possible side effects of ADMELOG?
ADMELOG may cause serious side effects that can lead to death, including:

- low blood sugar (hypoglycemia).Signs and symptoms that may indicate low blood sugar include:

- dizziness or light-headedness
- headache
- shakiness
- irritability or mood changes

- sweating
- blurred vision
- fast heartbeat
- hunger

- confusion
- slurred speech
- anxiety

- serious allergic reactions (whole body reaction). Get medical help right away, if you have any of these signs or symptoms of a severe allergic reaction:

- a rash over your whole body
- a fast heartbeat
- sweating

- trouble breathing
- feel faint

- low potassium in your blood (hypokalemia).
- heart failure.Taking certain diabetes pills called TZDs (thiazolidinediones) with ADMELOG may cause heart failure in some people. This can happen even if you have never had heart failure or heart problems before. If you already have heart failure it may get worse while you take TZDs with ADMELOG. Your healthcare provider should monitor you closely while you are taking TZDs with ADMELOG. Tell your healthcare provider if you have any new or worse symptoms of heart failure including:
  - shortness of breath
  - swelling of your ankles or feet
  - sudden weight gain.
  Treatment with TZDs and ADMELOG may need to be adjusted or stopped by your healthcare provider if you have new or worse heart failure.
- sudden onset of high blood sugar (hyperglycemia) and high amounts of ketones in the blood or urine (ketoacidosis) due to insulin pump problems.If ADMELOG is given through an insulin pump and the pump is not working the right way or in case of handling errors, you may not get the right amount of insulin, which can cause a sudden onset of high blood sugar and high amounts of ketones in the blood or urine.

Get emergency medical help if you have:

- trouble breathing
- swelling of your face, tongue, or throat
- dizziness

- shortness of breath
- sweating
- confusion

- fast heartbeat
- extreme drowsiness

The most common side effects of ADMELOG include:

- low blood sugar (hypoglycemia), allergic reactions, including reactions at the injection site, skin thickening or pits at the injection site (lipodystrophy), itching, and rash.

These are not all the possible side effects of ADMELOG.Call your doctor for medical advice about side effects. You may report side effects to FDA at 1-800-FDA-1088.

General information about the safe and effective use of ADMELOG.
Medicines are sometimes prescribed for purposes other than those listed in a Patient Information leaflet. Do notuse ADMELOG for a condition for which it was not prescribed. Do notgive ADMELOG to other people, even if they have the same symptoms that you have. It may harm them.
You can ask your pharmacist or healthcare provider for information about ADMELOG that is written for health professionals. For more information, go to www.sanofi.com or call 1-800-633-1610.

What are the ingredients in ADMELOG?
Active ingredient:insulin lispro
Inactive ingredients:dibasic sodium phosphate, glycerin, metacresol, water for injection, and zinc oxide (zinc ion). Hydrochloric acid and/or sodium hydroxide may be added to adjust pH.

ADMELOG and SoloStar are registered trademarks of sanofi-aventis U.S. LLC.
©2025 sanofi-aventis U.S. LLC.

This Patient Information has been approved by the U.S. Food and Drug Administration.

Revised: May2025

Repackaged and Distributed By:

Remedy Repack, Inc.

625 Kolter Dr. Suite #4 Indiana, PA 1-724-465-8762

INSTRUCTIONS FOR USE
ADMELOG®[ad-mah-log]
(insulin lispro)
injection, for subcutaneous use
10 mL or 3 mL Vial (100 units/mL, U-100)

Read this Instructions for Use before you start using ADMELOG and each time you get a new ADMELOG vial. There may be new information. This information does not take the place of talking to your healthcare provider about your medical condition or your treatment.

Do not share your ADMELOG syringes with other people, even if the needle has been changed. You may give other people a serious infection or get a serious infection from them.

Supplies needed to give your injection

- an ADMELOG 10 mL or 3 mL vial
- a U-100 insulin syringe and needle
- 2 alcohol swabs
- 1 sharps container for throwing away used needles and syringes. See " Disposing of used needles and syringes"at the end of these instructions.

Preparing your ADMELOG dose

- Wash your hands with soap and water or with alcohol.
- Check the ADMELOG label to make sure you are taking the right type of insulin. This is especially important if you use more than 1 type of insulin.
- Check the insulin to make sure it is clear and colorless. Do notuse ADMELOG if it is colored or cloudy, or if you see particles in the solution.
- Do notuse ADMELOG after the expiration date stamped on the label or 28 days after you first use it.
- Always use a syringe that is marked for U-100 insulin.If you use a syringe other than a U-100 insulin syringe, you may get the wrong dose of insulin.
- Always use a new syringe or needle for each injection to help ensure sterility and prevent blocked needles. Do not reuse or share your syringes or needles with other people. You may give other people a serious infection or get a serious infection from them.

Step 1:

If you are using a new vial, remove the protective cap. Do notremove the stopper.

Step 2:

Wipe the top of the vial with an alcohol swab. You do not have to shake the vial of ADMELOG before use.

Step 3:

Draw air into the syringe equal to your insulin dose. Put the needle through the rubber top of the vial and push the plunger to inject the air into the vial.

Step 4:

Leave the syringe in the vial and turn both upside down. Hold the syringe and vial firmly in one hand. Make sure the tip of the needle is in the insulin. With your free hand, pull the plunger to withdraw the correct dose into the syringe.

Step 5:

Before you take the needle out of the vial, check the syringe for air bubbles. If bubbles are in the syringe, hold the syringe straight up and tap the side of the syringe until the bubbles float to the top. Push the bubbles out with the plunger and draw insulin back in until you have the correct dose.

Step 6:

Remove the needle from the vial. Do not let the needle touch anything. You are now ready to inject.

Giving your ADMELOG injection with a syringe

- Inject your insulin exactly as your healthcare provider has shown you.
- ADMELOG starts acting fast,so give your injection within 15 minutes before or right after you eat a meal.

Step 7:

- Choose your injection site: ADMELOG is injected under the skin (subcutaneously) of your upper arms, thighs, buttocks, or stomach area (abdomen).
- Change (rotate) your injection sites within the area you choose for each doseto reduce your risk of getting pits in the skin or thickened skin (lipodystrophy) and skin with lumps (localized cutaneous amyloidosis) at the injection sites.
- Do notinject where the skin has pits, is thickened, or has lumps.
- Do notinject where the skin is tender, bruised, scaly or hard, or into scars or damaged skin.

- Wipe the skin with an alcohol swab to clean the injection site. Let the injection site dry before you inject your dose.

Step 8:

- Pinch the skin.
- Insert the needle in the way your healthcare provider showed you.
- Release the skin.
- Slowly push in the plunger of the syringe all the way, making sure you have injected all the insulin.
- Leave the needle in the skin for about 10seconds.

Step 9:

- Pull the needle straight out of your skin.
- Gently press the injection site for several seconds. Do notrub the area.
- Do notrecap the used needle. Recapping the needle can lead to a needle-stick injury.

Giving your ADMELOG using an insulin pump

- If you have been prescribed an insulin pump, check the pump manufacturer's user manual to see if ADMELOG can be used with the pump.
- ADMELOG should be given into an area of your body recommended in the instructions that come with your insulin pump.
- Change your insertion site according to the manufacturer's user manual.
- Change (rotate) your insertion sites within the area you choose for each insertionto reduce your risk of getting pits in skin or thickened skin (lipodystrophy) and skin with lumps (localized cutaneous amyloidosis) at the injection sites. Do notinsert into the exact same spot for each injection. Do notinsert where the skin has pits, is thickened, or has lumps. Do notinsert where the skin is tender, bruised, scaly or hard, or into scars or damaged skin.
- Call your healthcare provider and choose a new infusion site if the skin at the infusion site becomes red, itchy, or thickened.
- Your healthcare provider should provide recommendations for appropriate pump basal and meal-time infusion rates. Call your healthcare provider if you have any questions about using the insulin pump.
- Change the insulin in the reservoir at least every 7 days or according to the pump user manual, whichever is shorter, even if you have not used all of the insulin.
- Do notdilute or mix ADMELOG with any other type of insulin in your insulin pump.
- You should be trained on how to give insulin by injection and have an alternative insulin delivery system in case of pump failure.
- When you start using ADMELOG by infusion pump, your insulin dose may need to be changed. Check with your healthcare provider before making any changes to your insulin dose.

Disposing of used needles and syringes

- Put your used needles and syringes in a FDA-cleared sharps disposal container right away after use. Do notthrow away (dispose of) loose needles and syringes in your household trash.
- If you do not have a FDA-cleared sharps container, you may use a household container that is:
  - made of a heavy-duty plastic,
  - can be closed with a tight-fitting, puncture-resistant lid, without sharps being able to come out,
  - upright and stable during use,
  - leak resistant, and
  - properly labeled to warn of hazardous waste inside the container.
- When your sharps disposal container is almost full, you will need to follow your community guidelines for the right way to dispose of your sharps disposal container. There may be state or local laws about how you should throw away used needles and syringes. For more information about safe sharps disposal, and for specific information about sharps disposal in the state that you live in, go to the FDA's website at: http://www.fda.gov/safesharpsdisposal.
- Do notdispose of your used sharps disposal container in your household trash unless your community guidelines permit this. Do notrecycle your used sharps disposal container.

How should I store ADMELOG?

Unopened (not in-use) ADMELOG vials

- Store unused ADMELOG vials in the refrigerator from 36°F to 46°F (2°C to 8°C).
- Do notfreeze ADMELOG.
- Keep ADMELOG away from direct heat and light.
- If a vial has been frozen or overheated, throw it away.
- Unopened vials can be used until the expiration date on the carton and label if they have been stored in the refrigerator.
- Unopened vials should be thrown away after 28 days if they are stored at room temperature.

After ADMELOG vials have been opened (in-use)

- Store in-use (opened) ADMELOG vials in a refrigerator from 36°F to 46°F (2°C to 8°C) or at room temperature up to 86°F (30°C) for up to 28 days.
- Do notfreeze ADMELOG.
- Keep ADMELOG out of direct heat and light.
- If a vial has been frozen, throw it away.
- The ADMELOG vial you are using should be thrown away after 28days, even if it still has insulin left in it.

ADMELOG in an insulin pump

- Throw away ADMELOG in the pump reservoir if it has been exposed to temperatures higher than 98.6°F (37°C). This may happen if the pump housing, cover, tubing, or sport case is exposed to sunlight or direct heat.

Keep ADMELOG vials, syringes, needles and all medicines out of the reach of children.

ADMELOG is a registered trademark of sanofi-aventis U.S. LLC.
©2025 sanofi-aventis U.S. LLC.

This Instructions for Use has been approved by the U.S. Food and Drug Administration.

Revised: May 2025

Repackaged and Distributed By:

Remedy Repack, Inc.

625 Kolter Dr. Suite #4 Indiana, PA 1-724-465-8762

INSTRUCTIONS FOR USE

ADMELOG®SoloStar®[ad-mah-log]
(insulin lispro)
injection, for subcutaneous use
3 mL single-patient-use prefilled pen (100 units/mL, U-100)

Read this first

Do not share your ADMELOG SoloStar pen with other people, even if the needle has been changed. You may give other people a serious infection, or get a serious infection from them.

People who are blind or have vision problems should not use ADMELOG SoloStar prefilled pen without help from a person trained to use ADMELOG SoloStar prefilled pen.

ADMELOG SoloStar is a disposable prefilled pen used to inject ADMELOG. Each ADMELOG SoloStar has 300 units of insulin which can be used for multiple injections. You can select doses from 1 to 80 units in steps of 1 unit. The pen plunger moves with each dose. The plunger will only move to the end of the cartridge when 300 units of insulin have been given.

Important information

- Do notuse your pen if it is damaged or if you are not sure that it is working properly.
- Do notuse a syringe to remove insulin from your pen.
- Do not reuse needles.If you do, you might get the wrong dose of ADMELOG and/or increase the chance of getting an infection.
- Always perform a safety test (see Step 3).
- Always carry a spare pen and spare needles in case they get lost or stop working.
- Change (rotate) your injection sites within the area you choose for each dose (see " Places to inject").

Learn to inject

- Talk with your healthcare provider about how to inject before using your pen.
- Ask for help if you have problems handling the pen, for example if you have problems with your sight.
- Read all of these instructions before using your pen. If you do not follow all of these instructions, you may get too much or too little insulin.

Need help?

If you have any questions about your pen or about diabetes, ask your healthcare provider, or go to www.Admelog.com or call sanofi-aventis at 1-800-633-1610.

Extra items you will need:

- a new sterile needle (see Step 2).
- an alcohol swab.
- a puncture-resistant container for used needles and pens. (See " Throwing your pen away)

Places to inject

- Inject your insulin exactly as your healthcare provider has shown you.
- Inject your insulin under the skin (subcutaneously) of your upper legs (thighs), upper arms, buttocks or stomach area (abdomen).
- Change (rotate) your injection sites within the area you choose for each dose to reduce your risk of getting pits in skin or thickened skin (lipodystrophy) and skin with lumps (localized cutaneous amyloidosis) at the injection sites.
- Do notinject where the skin has pits, is thickened, or has lumps.
  Do notinject where the skin is tender, bruised, scaly or hard, or into scars or damaged skin.

Get to know your pen

Step 1: Check your pen

Take a new pen out of the refrigerator at least 1hour before you inject. Cold insulin is more painful to inject.

1A Check the name and expiration date on the label of your pen.

- Make sure you have the correct insulin.
- Do notuse your pen after the expiration date.

1B Pull off the pen cap.

1C Check that the insulin is clear.

- Do notuse the pen if the insulin looks cloudy, colored or contains particles.

1D Wipe the rubber seal with an alcohol swab.

If you have other injector pens:

- Making sure you have the correct medicine is especially important if you have other injector pens.

Step 2: Attach a new needle

- Do notreuse needles. Always use a new sterile needle for each injection. This helps stop blocked needles, contamination, and infection.
- Only use needles that are compatible for use with ADMELOG SoloStar, such as needles from BD (such as BD Ultra-Fine), Ypsomed (such as Clickfine), Owen Mumford (such as Unifine Pentips).

2A Take a new needle and peel off the protective seal.

2B Keep the needle straight and screw it onto the pen until fixed. Do not over-tighten.

2C Pull off the outer needle cap. Keep this for later.

2D Pull off the inner needle cap and throw away.

Handling needles:

- Take care when handling needles to prevent needle-stick injury and cross-infection.

Step 3: Do a safety test

Always do a safety test before each injection to:

- Check your pen and the needle to make sure they are working properly.
- Make sure that you get the correct insulin dose.

3A Select 2 units by turning the dose selector until the dose pointer is at the 2 mark.

3B Press the injection button all the way in.

- When insulin comes out of the needle tip, your pen is working correctly.

If no insulin appears:

- You may need to repeat this step up to 3 times before seeing insulin.
- If no insulin comes out after the third time, the needle may be blocked. If this happens:
  - change the needle (see Step 6and Step 2),
  - then repeat the safety test (Step 3).
- Do notuse your pen if there is still no insulin coming out of the needle tip. Use a new pen.
- Do notuse a syringe to remove insulin from your pen.

If you see air bubbles:

- You may see air bubbles in the insulin. This is normal, they will not harm you.

Step 4: Select the dose

Do notselect a dose or press the injection button without a needle attached. This may damage your pen.

4A Make sure a needle is attached and the dose is set to "0."

4B Turn the dose selector until the dose pointer lines up with your dose.

- If you turn past your dose, you can turn back down.
- If there are not enough units left in your pen for your dose, the dose selector will stop at the number of units left.
- If you cannot select your full prescribed dose, use a new pen or inject the remaining units and use a new pen to complete your dose.

How to read the dose window

Even numbers are shown in line with dose pointer.

20 units selected

Odd numbers are shown as a line between even numbers.

21 units selected

Units of insulin in your pen:

- Your pen contains a total of 300units of insulin. You can select doses from 1to 80units in steps of 1unit. Each pen contains more than 1 dose.
- You can see roughly how many units of insulin are left by looking at where the plunger is on the insulin scale.

Step 5: Inject your dose

If you find it hard to press the injection button in, do notforce it as this may break your pen. See the section below for help.

5A Choose a place to inject as shown in the picture above.

5B Push the needle into your skin as shown by your healthcare provider.

- Do not touch the injection button yet.

5C Place your thumb on the injection button. Then press all the way in and hold.

- Do notpress at an angle. Your thumb could block the dose selector from turning.

5D Keep the injection button held in and when you see "0" in the dose window, slowly count to 10.

- This will make sure you get your full dose.

5E After holding and slowly counting to 10, release the injection button. Then remove the needle from your skin.

If you find it hard to press the button in:

- Change the needle (see Step 6and Step 2) then do a safety test (see Step 3).
- If you still find it hard to press in, get a new pen.
- Do notuse a syringe to remove insulin from your pen.

Step 6: Remove the needle

- Take care when handling needles to prevent needle-stick injury and cross-infection.
- Do notput the inner needle cap back on.

6A Grip the widest part of the outer needle cap. Keep the needle straight and guide it into the outer needle cap. Then push firmly on.

- The needle can puncture the cap if it is recapped at an angle.

6B Grip and squeeze the widest part of the outer needle cap. Turn your pen several times with your other hand to remove the needle.

- Try again if the needle does not come off the first time.

6C Throw away the used needle in a puncture-resistant container(see " Throwing your pen away" at the end of this Instructions for Use).

6D Put your pen cap back on.

- Do not put the pen back in the refrigerator.

How to store your pen

Before first use

- Keep new pens in the refrigerator between 36°F to 46°F (2°C to 8°C).
- Do notfreeze. Do notuse ADMELOG if it has been frozen.

After first use

- Keep your pen at room temperature up to 86°F (30°C).
- Keep your pen away from heat or light.
- Store your pen with the pen cap on.
- Do notput your pen back in the refrigerator.
- Do notstore your pen with the needle attached.
- Keep out of the reach of children.
- Only use your pen for up to 28 daysafter its first use. Throw away the ADMELOG SoloStar pen you are using after 28 days, even if it still has insulin left in it.

How to care for your pen

Handle your pen with care

- Do not drop your pen or knock it against hard surfaces.
- If you think that your pen may be damaged, do nottry to fix it. Use a new one.

Protect your pen from dust and dirt

- You can clean the outside of your pen by wiping it with a damp cloth (water only). Do notsoak, wash or lubricate your pen. This may damage it.

Throwing your pen and used needle pen away

- The used ADMELOG SoloStar pen may be thrown away in your household trash after you have removed the needle.
- Put the used needle in a FDA-cleared sharps disposal container right away after use. Do notthrow away (dispose of) the used needles in your household trash.
- If you do not have a FDA-cleared sharps disposal container, you may use a household container that is:
  - made of a heavy-duty plastic,
  - can be closed with a tight-fitting, puncture-resistant lid, without sharps being able to come out,
  - upright and stable during use,
  - leak-resistant, and
  - properly labeled to warn of hazardous waste inside the container.
- When your sharps disposal container is almost full, you will need to follow your community guidelines for the right way to dispose of your sharps disposal container. There may be state or local laws about how you should throw away used needles and syringes. For more information about safe sharps disposal, and for specific information about sharps disposal in the state that you live in, go to the FDA's website at: http://www.fda.gov/safesharpsdisposal.

ADMELOG and SoloStar are registered trademarks of sanofi-aventis U.S. LLC.
©2025 sanofi-aventis U.S. LLC.
Other brands listed are the registered trademarks of their respective owners and are not trademarks of sanofi-aventis U.S. LLC.

This Instructions for Use has been approved by the U.S. Food and Drug Administration.

Revised: May 2025

Repackaged and Distributed By:

Remedy Repack, Inc.

625 Kolter Dr. Suite #4 Indiana, PA 1-724-465-8762

PACKAGE LABEL

DRUG: ADMELOG

GENERIC: insulin lispro

DOSAGE: INJECTION, SOLUTION

ADMINSTRATION: SUBCUTANEOUS

NDC: 70518-4275-0

PACKAGING: 3 mL in 1 SYRINGE

OUTER PACKAGING: 5 in 1 CARTON

ACTIVE INGREDIENT(S):

- INSULIN LISPRO 100U in 1mL

INACTIVE INGREDIENT(S):

- GLYCERIN
- SODIUM PHOSPHATE, DIBASIC, UNSPECIFIED FORM
- METACRESOL
- ZINC OXIDE
- WATER
- HYDROCHLORIC ACID
- SODIUM HYDROXIDE